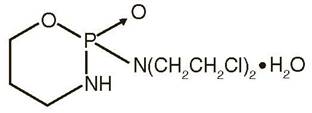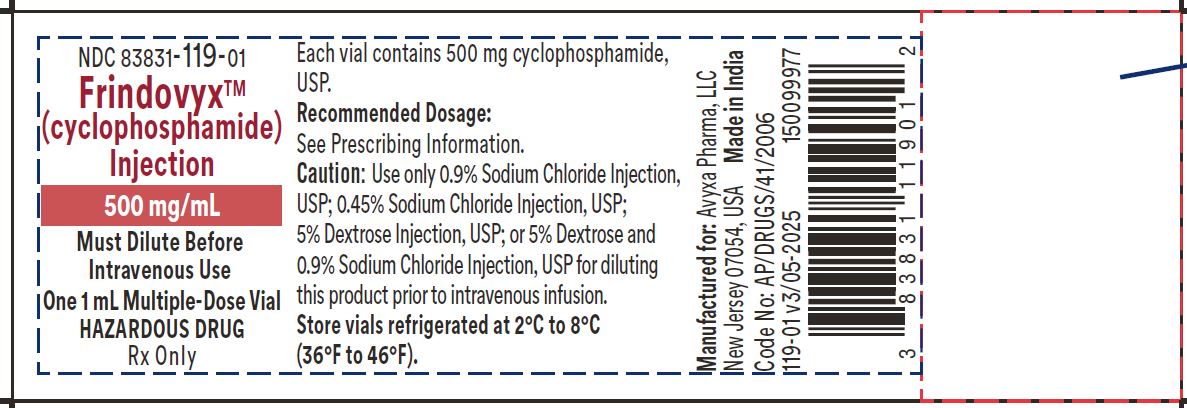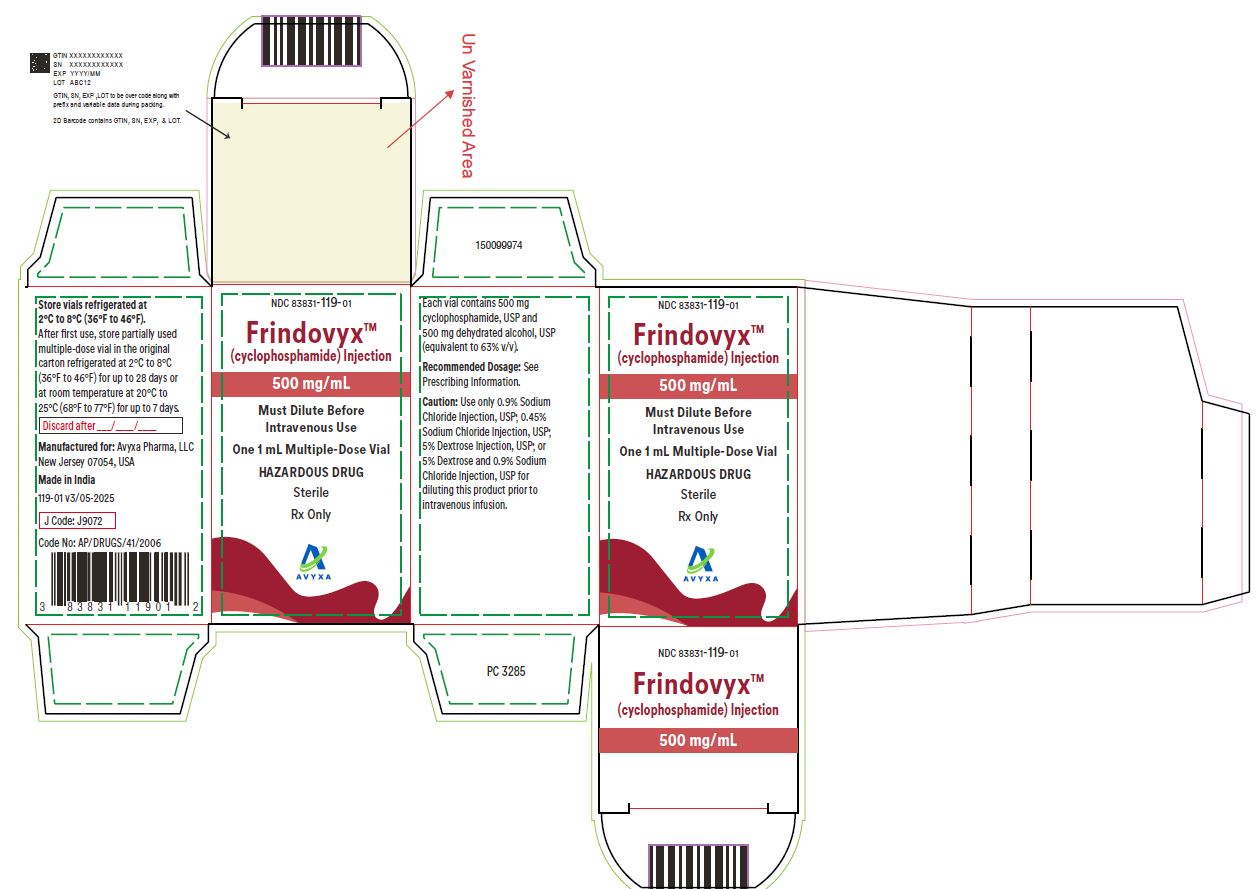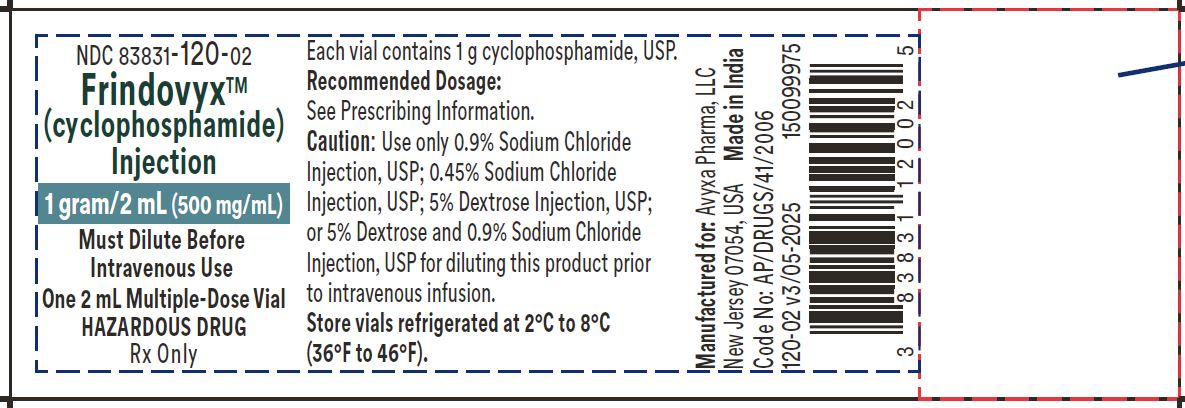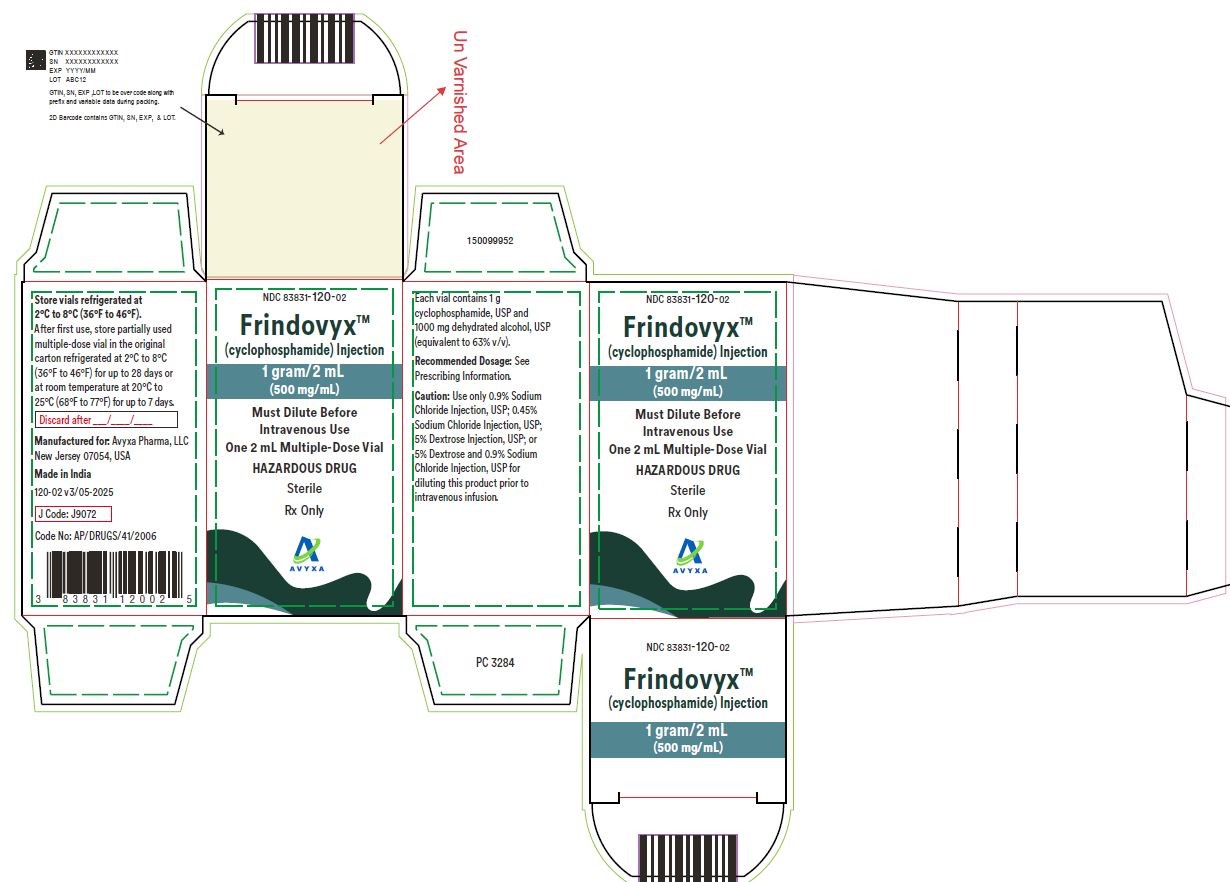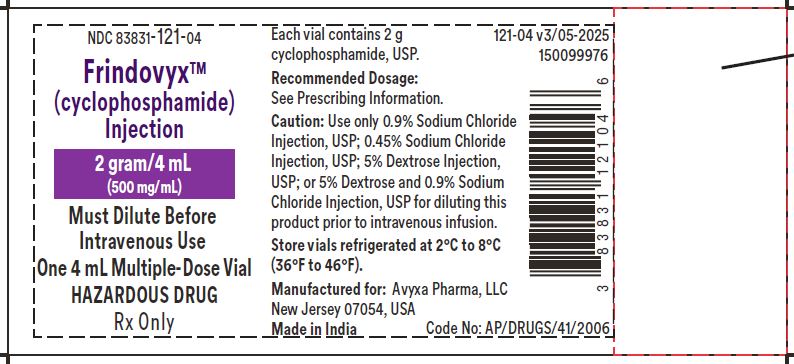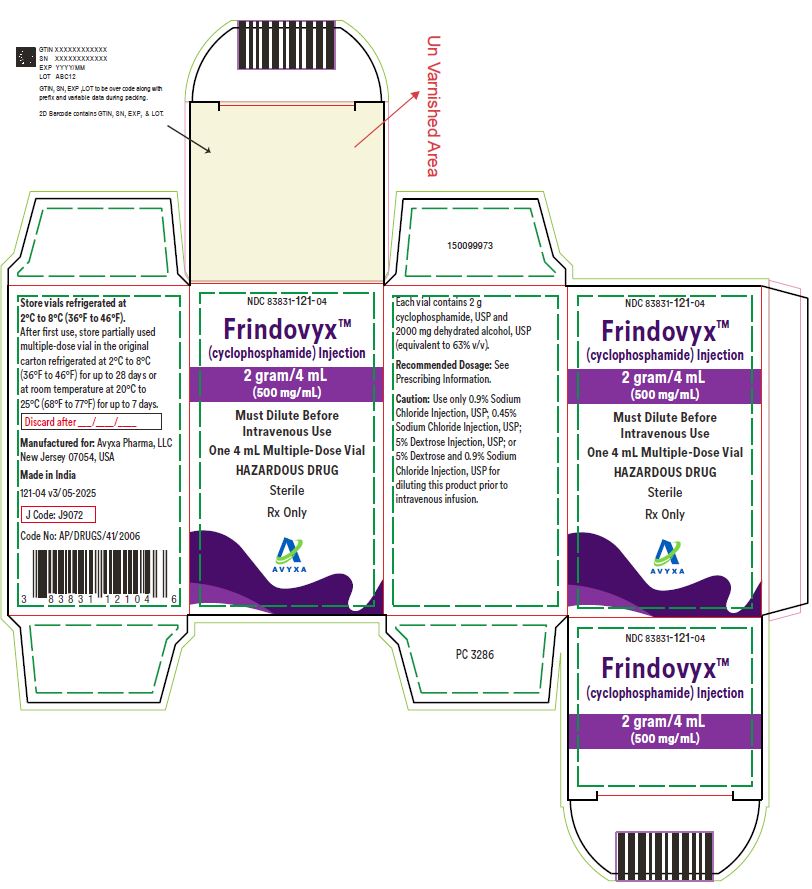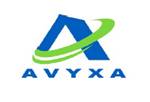 DRUG LABEL: Frindovyx
NDC: 83831-119 | Form: INJECTION
Manufacturer: Avyxa Pharma, LLC
Category: prescription | Type: HUMAN PRESCRIPTION DRUG LABEL
Date: 20250811

ACTIVE INGREDIENTS: CYCLOPHOSPHAMIDE 500 mg/1 mL
INACTIVE INGREDIENTS: DEHYDRATED ALCOHOL

HIGHLIGHTS OF PRESCRIBING INFORMATION

These highlights do not include all the information needed to use FRINDOVYX safely and effectively. See full prescribing information for FRINDOVYX.
FRINDOVYXTM (cyclophosphamide) injection, for intravenous use
Initial U.S. Approval: 1959

RECENT MAJOR CHANGES

Dosage and Administration (2.3) 7/2025

1 INDICATIONS AND USAGE

FRINDOVYX is an alkylating drug indicated for treatment of adults and pediatric patients with:

- Malignant Diseases: malignant lymphomas: Hodgkin's disease, lymphocytic lymphoma, mixed-cell type lymphoma, histiocytic lymphoma, Burkitt's lymphoma; multiple myeloma, leukemias, mycosis fungoides, neuroblastoma, adenocarcinoma of ovary, retinoblastoma, breast carcinoma (1)

2 DOSAGE AND ADMINISTRATION

During or immediately after FRINDOVYX administration, administer adequate amounts of fluid to reduce the risk of urinary tract toxicity (2.1).

Malignant Diseases: Adult and Pediatric Patients (2.2)

- Intravenous: Initial course for patients with no hematologic deficiency: 40 mg/kg to 50 mg/ kg in divided doses over 2 to 5 days. Other regimens include 10 mg/kg to 15 mg/kg given every 7 to 10 days or 3 mg/kg to 5 mg/kg twice weekly. (2.2)
- See full prescribing information for instructions on preparation, handling, and administration. (2.3)

3 DOSAGE FORMS AND STRENGTHS

- Injection: 500 mg/mL, 1 g/2 mL (500 mg/mL), and 2 g/4mL (500 mg/mL) in multiple-dose vial (3)

4 CONTRAINDICATIONS

- Hypersensitivity to cyclophosphamide (4)
- Urinary outflow obstruction (4)

5 WARNINGS AND PRECAUTIONS

- Myelosuppression, Immunosuppression, Bone Marrow Failure and Infections: Severe immunosuppression may lead to serious and sometimes fatal infections. Close hematological monitoring is required. (5.1)
- Urinary Tract and Renal Toxicity: Hemorrhagic cystitis, pyelitis, ureteritis, and hematuria can occur. Urotoxicity can be fatal. Exclude or correct any urinary tract obstructions prior to treatment. (5.2)
- Cardiotoxicity: Myocarditis, myopericarditis, pericardial effusion, arrhythmias and congestive heart failure, which may be fatal, have been reported. Monitor patients, especially those with risk factors for cardiotoxicity or pre-existing cardiac disease. (5.3)
- Pulmonary Toxicity: Pneumonitis, pulmonary fibrosis and pulmonary veno-occlusive disease leading to respiratory failure may occur. Monitor patients for signs and symptoms of pulmonary toxicity. (5.4)
- Secondary malignancies(5.5)
- Veno-occlusive Liver Disease: Fatal outcome can occur. (5.6)
- Alcohol content: The alcohol content in a dose of FRINDOVYX may affect the central nervous system. This may include impairment of a patient's ability to drive or use machines immediately after infusion. (5.7)
- Embryo-Fetal Toxicity: Can cause fetal harm. Advise patients of reproductive potential of the potential risk to a fetus and to use effective contraception. (5.8, 8.1, 8.3)

6 ADVERSE REACTIONS

Adverse reactions reported most often include neutropenia, febrile neutropenia, fever, alopecia, nausea, vomiting, and diarrhea. (6.1)

To report SUSPECTED ADVERSE REACTIONS, contact Avyxa Pharma, LLC at 1-888-520-0954 or FDA at 1-800-FDA-1088 or www.fda.gov/medwatch.

8 USE IN SPECIFIC POPULATIONS

- Lactation: Advise not to breastfeed. (8.2)
- Renal Impairment: Monitor for toxicity in patients with moderate and severe renal impairment. (8.6, 12.3)

FULL PRESCRIBING INFORMATION

1 INDICATIONS AND USAGE

Malignant Diseases

FRINDOVYX is indicated for the treatment of adult and pediatric patients with:

- malignant lymphomas (Stages III and IV of the Ann Arbor staging system), Hodgkin's disease, lymphocytic lymphoma (nodular or diffuse), mixed-cell type lymphoma, histiocytic lymphoma Burkitt's lymphoma
- multiple myeloma
- leukemias: chronic lymphocytic leukemia, chronic granulocytic leukemia (it is usually ineffective in acute blastic crisis), acute myelogenous and monocytic leukemia, acute lymphoblastic (stem-cell) leukemia (cyclophosphamide given during remission is effective in prolonging its duration)
- mycosis fungoides (advanced disease)
- neuroblastoma (disseminated disease)
- adenocarcinoma of the ovary
- retinoblastoma
- carcinoma of the breast

Cyclophosphamide, although effective alone in susceptible malignancies, is more frequently used concurrently or sequentially with other antineoplastic drugs.

2 DOSAGE AND ADMINISTRATION

2.1 Important Administration Instructions

During or immediately after the administration of FRINDOVYX, adequate amounts of fluid should be ingested or infused to force diuresis in order to reduce the risk of urinary tract toxicity. Therefore, FRINDOVYX should be administered in the morning.

2.2 Recommended Dosage for Malignant Diseases

Adults and Pediatric Patients

Intravenous

When used as the only oncolytic drug therapy, the recommended dosage for the initial course of FRINDOVYX for patients with no hematologic deficiency is 40 mg/kg to 50 mg/kg given intravenously in divided doses over a period of 2 to 5 days. Other intravenous regimens include 10 mg/kg to 15 mg/kg given every 7 to 10 days or 3 mg/kg to 5 mg/kg twice weekly.

Adjust the dosage of FRINDOVYX based on the specific regimen administered, response to treatment, myelosuppression or other adverse reactions, and patient risk factors [see Warnings and Precautions (5)].

2.3 Preparation, Handling and Administration

FRINDOVYX is a hazardous drug. Follow applicable special handling and disposal procedures^1. Caution should be exercised when handling and preparing FRINDOVYX. To minimize the risk of dermal exposure, always wear gloves when handling vials containing FRINDOVYX.

FRINDOVYX

Intravenous Administration

Parenteral drug products should be inspected visually for particulate matter and discoloration prior to administration, whenever solution and container permit. Do not use cyclophosphamide vials if there are signs of particulate matter.

Cyclophosphamide does not contain any antimicrobial preservative and thus care must be taken to assure the sterility of prepared solutions. Use aseptic technique.

For Direct Intravenous Injection

Withdraw the prescribed dose of FRINDOVYX from the vial with a syringe and dilute with 0.9% Sodium Chloride Injection, USP to a concentration of 20 mg/mL of cyclophosphamide.

For Intravenous Infusion

Withdraw the prescribed dose of FRINDOVYX from the vial with a syringe and dilute FRINDOVYX to a concentration of 2 mg/mL with any of the following diluents:

- 0.9% Sodium Chloride Injection, USP

- 0.45% Sodium Chloride Injection, USP
- 5% Dextrose Injection, USP
- 5% Dextrose and 0.9% Sodium Chloride Injection, USP

To reduce the likelihood of adverse reactions that appear to be administration rate-dependent (e.g., facial swelling, headache, nasal congestion, scalp burning), cyclophosphamide should be injected or infused very slowly. Duration of the infusion also should be appropriate for the volume and type of carrier fluid to be infused.

Storage of Diluted Cyclophosphamide Solution:

If not used immediately, for microbiological integrity, cyclophosphamide solutions should be stored as described in Table 1.

Table 1: Storage of Cyclophosphamide Solutions
Diluent | Storage
Diluent | Room Temperature | Refrigerated
Diluted Solution (20 mg/mL) for Direct Intravenous Injection
0.9% Sodium Chloride Injection, USP | up to 24 hours | up to 6 days
Diluted Solutions (2 mg/mL) for Intravenous Infusion
0.9% Sodium Chloride Injection, USP | up to 24 hours | up to 6 days
0.45% Sodium Chloride Injection, USP | up to 24 hours | up to 6 days
5% Dextrose Injection, USP | up to 24 hours | up to 36 hours
5% Dextrose and 0.9% Sodium Chloride Injection, USP | up to 24 hours | up to 36 hours

Storage of Undiluted Cyclophosphamide Solution (Multiple-Dose Vial):

After first use, store partially used multiple-dose vial in the original carton refrigerated at 2°C to 8°C (36ºF to 46°F) for up to 28 days or at room temperature at 20°C to 25°C (68ºF to 77°F) for up to 7 days. Discard unused portion.

3 DOSAGE FORMS AND STRENGTHS

FRINDOVYX: Clear, colorless or slight yellow, sterile solution of cyclophosphamide in multiple-dose vial in the following three strengths.

- 500 mg/mL
- 1 g/2 mL (500 mg/mL)
- 2 g/4 mL (500 mg/mL)

4 CONTRAINDICATIONS

Hypersensitivity

FRINDOVYX is contraindicated in patients who have a history of severe hypersensitivity reactions to cyclophosphamide, any of its metabolites, or to other components of the product. Anaphylactic reactions including death have been reported with cyclophosphamide. Cross-sensitivity with other alkylating agents can occur.

Urinary Outflow Obstruction

FRINDOVYX is contraindicated in patients with urinary outflow obstruction [see Warnings and Precautions (5.2)].

5 WARNINGS AND PRECAUTIONS

5.1 Myelosuppression, Immunosuppression, Bone Marrow Failure and Infections

Cyclophosphamide can cause myelosuppression (leukopenia, neutropenia, thrombocytopenia and anemia), bone marrow failure, and severe immunosuppression which may lead to serious and sometimes fatal infections, including sepsis and septic shock. Latent infections can be reactivated [see Adverse Reactions (6)].

Antimicrobial prophylaxis may be indicated in certain cases of neutropenia at the discretion of the managing physician. In case of neutropenic fever, antibiotic therapy is indicated. Antimycotics and/or antivirals may also be indicated.

Monitoring of complete blood counts is essential during cyclophosphamide treatment so that the dose can be adjusted, if needed. Cyclophosphamide should not be administered to patients with neutrophils ≤1,500/mm^3 and platelets < 50,000/mm^3. Cyclophosphamide treatment may not be indicated, or should be interrupted, or the dose reduced, in patients who have or who develop a serious infection. G-CSF may be administered to reduce the risks of neutropenia complications associated with cyclophosphamide use. Primary and secondary prophylaxis with G-CSF should be considered in all patients considered to be at increased risk for neutropenia complications. The nadirs of the reduction in leukocyte count and thrombocyte count are usually reached in weeks 1 and 2 of treatment. Peripheral blood cell counts are expected to normalize after approximately 20 days. Bone marrow failure has been reported. Severe myelosuppression may be expected particularly in patients pretreated with and/or receiving concomitant chemotherapy and/or radiation therapy.

5.2 Urinary Tract and Renal Toxicity

Hemorrhagic cystitis, pyelitis, ureteritis, and hematuria have been reported with cyclophosphamide. Medical and/or surgical supportive treatment may be required to treat protracted cases of severe hemorrhagic cystitis. Discontinue cyclophosphamide therapy in case of severe hemorrhagic cystitis.

Urotoxicity (bladder ulceration, necrosis, fibrosis, contracture and secondary cancer) may require interruption of cyclophosphamide treatment or cystectomy. Urotoxicity can be fatal. Urotoxicity can occur with short-term or long-term use of cyclophosphamide.

Before starting treatment, exclude or correct any urinary tract obstructions [see Contraindications (4)]. Urinary sediment should be checked regularly for the presence of erythrocytes and other signs of urotoxicity and/or nephrotoxicity. Cyclophosphamide should be used with caution, if at all, in patients with active urinary tract infections. Aggressive hydration with forced diuresis and frequent bladder emptying can reduce the frequency and severity of bladder toxicity. Mesna has been used to prevent severe bladder toxicity.

5.3 Cardiotoxicity

Myocarditis, myopericarditis, pericardial effusion including cardiac tamponade, and congestive heart failure, which may be fatal, have been reported with cyclophosphamide therapy.

Supraventricular arrhythmias (including atrial fibrillation and flutter) and ventricular arrhythmias (including severe QT prolongation associated with ventricular tachyarrhythmia) have been reported after treatment with regimens that included cyclophosphamide.

The risk of cardiotoxicity may be increased with high doses of cyclophosphamide, in patients with advanced age, and in patients with previous radiation treatment to the cardiac region and/or previous or concomitant treatment with other cardiotoxic agents.

Particular caution is necessary in patients with risk factors for cardiotoxicity and in patients with pre-existing cardiac disease.

Monitor patients with risk factors for cardiotoxicity and with pre-existing cardiac disease.

5.4 Pulmonary Toxicity

Pneumonitis, pulmonary fibrosis, pulmonary veno-occlusive disease and other forms of pulmonary toxicity leading to respiratory failure have been reported during and following treatment with cyclophosphamide. Late onset pneumonitis (greater than 6 months after start of cyclophosphamide) appears to be associated with increased mortality. Pneumonitis may develop years after treatment with cyclophosphamide.

Monitor patients for signs and symptoms of pulmonary toxicity.

5.5 Secondary Malignancies

Cyclophosphamide is genotoxic [see Nonclinical Toxicology (13.1)]. Secondary malignancies (urinary tract cancer, myelodysplasia, acute leukemias, lymphomas, thyroid cancer, and sarcomas) have been reported in patients treated with cyclophosphamide-containing regimens. The risk of bladder cancer may be reduced by prevention of hemorrhagic cystitis.

5.6 Veno-occlusive Liver Disease

Veno-occlusive liver disease (VOD) including fatal outcome has been reported in patients receiving cyclophosphamide-containing regimens. A cytoreductive regimen in preparation for bone marrow transplantation that consists of cyclophosphamide in combination with whole-body irradiation, busulfan, or other agents has been identified as a major risk factor. VOD has also been reported to develop gradually in patients receiving long-term low-dose immunosuppressive doses of cyclophosphamide. Other risk factors predisposing to the development of VOD include preexisting disturbances of hepatic function, previous radiation therapy of the abdomen, and a low performance status.

5.7 Alcohol Content

The alcohol content in a dose of FRINDOVYX may affect the central nervous system and should be taken into account for patients in whom alcohol intake should be avoided or minimized. Consideration should be given to the alcohol content in FRINDOVYX on the ability to drive or use machines immediately after the infusion.

Each administration of FRINDOVYX at 50 mg per kg delivers 0.0448 g/kg of ethanol. For a 75 kg patient this would deliver 3.36 grams of ethanol [see Description (11)]. Other cyclophosphamide products may have a different amount of alcohol or no alcohol.

5.8 Embryo-Fetal Toxicity

Based on its mechanism of action and published reports of effects in pregnant patients or animals, FRINDOVYX can cause fetal harm when administered to a pregnant woman [see Use in Specific Populations (8.1), Clinical Pharmacology (12.1), and Nonclinical Toxicology (13.1)]. Exposure to cyclophosphamide during pregnancy may cause birth defects, miscarriage, fetal growth retardation, and fetotoxic effects in the newborn. Cyclophosphamide is teratogenic and embryo-fetal toxic in mice, rats, rabbits and monkeys.

Advise pregnant women and females of reproductive potential of the potential risk to the fetus [see Use in Specific Populations (8.1)]. Advise females of reproductive potential to use effective contraception during treatment with FRINDOVYX and for up to 1 year after completion of therapy. Advise male patients with female partners of reproductive potential to use effective contraception during treatment with FRINDOVYX and for 4 months after completion of therapy [see Use in Specific Populations (8.1, 8.3)].

5.9 Infertility

Male and female reproductive function and fertility may be impaired in patients being treated with FRINDOVYX. Cyclophosphamide interferes with oogenesis and spermatogenesis. It may cause sterility in both sexes. Development of sterility appears to depend on the dose of cyclophosphamide, duration of therapy, and the state of gonadal function at the time of treatment. Cyclophosphamide-induced sterility may be irreversible in some patients. Advise patients on the potential risks for infertility [see Use in Specific Populations (8.3 and 8.4)].

5.10 Impairment of Wound Healing

Cyclophosphamide may interfere with normal wound healing.

5.11 Hyponatremia

Hyponatremia associated with increased total body water, acute water intoxication, and a syndrome resembling SIADH (syndrome of inappropriate secretion of antidiuretic hormone), which may be fatal, has been reported.

6 ADVERSE REACTIONS

The following adverse reactions are discussed in more detail in other sections of the labeling.

- Hypersensitivity [see Contraindications (4)]
- Myelosuppression, Immunosuppression, Bone Marrow Failure, and Infections [see Warnings and Precautions (5.1)]
- Urinary Tract and Renal Toxicity [see Warnings and Precautions (5.2)]
- Cardiotoxicity [see Warnings and Precautions (5.3)]
- Pulmonary Toxicity [see Warnings and Precautions (5.4)]
- Secondary Malignancies [see Warnings and Precautions (5.5)]
- Veno-occlusive Liver Disease [see Warnings and Precautions (5.6)]
- Alcohol Content [see Warnings and Precautions (5.7)]
- Infertility [see Warnings and Precautions (5.9) and Use in Specific Populations (8.3 and 8.4)]
- Impaired Wound Healing [see Warnings and Precautions (5.10)]
- Hyponatremia [see Warnings and Precautions (5.11)]

6.1 Clinical Trials and Postmarketing Experience

The following adverse reactions associated with the use of cyclophosphamide were identified in clinical studies or postmarketing reports. Because some of these reactions were reported voluntarily from a population of uncertain size, it is not always possible to reliably estimate their frequency or establish a causal relationship to drug exposure.

The most common adverse reactions were neutropenia, febrile neutropenia, fever, alopecia, nausea, vomiting, and diarrhea.

Cardiac: cardiac arrest, ventricular fibrillation, ventricular tachycardia, cardiogenic shock, pericardial effusion (progressing to cardiac tamponade), myocardial hemorrhage, myocardial infarction, cardiac failure (including fatal outcomes), cardiomyopathy, myocarditis, pericarditis, carditis, atrial fibrillation, supraventricular arrhythmia, ventricular arrhythmia, bradycardia, tachycardia, palpitations, QT prolongation.

Congenital, Familial and Genetic: intra-uterine death, fetal malformation, fetal growth retardation, fetal toxicity (including myelosuppression, gastroenteritis).

Ear and Labyrinth: deafness, hearing impaired, tinnitus.

Endocrine: water intoxication.

Eye: visual impairment, conjunctivitis, lacrimation.

Gastrointestinal: gastrointestinal hemorrhage, acute pancreatitis, colitis, enteritis, cecitis, stomatitis, constipation, parotid gland inflammation, nausea, vomiting, diarrhea.

General Disorders and Administrative Site Conditions: multiorgan failure, general physical deterioration, influenza-like illness, injection/infusion site reactions (thrombosis, necrosis, phlebitis, inflammation, pain, swelling, erythema), pyrexia, edema, chest pain, mucosal inflammation, asthenia, pain, chills, fatigue, malaise, headache, febrile neutropenia.

Hematologic: myelosuppression, bone marrow failure, disseminated intravascular coagulation and hemolytic uremic syndrome (with thrombotic microangiopathy).

Hepatic: veno-occlusive liver disease, cholestatic hepatitis, cytolytic hepatitis, hepatitis, cholestasis; hepatotoxicity with hepatic failure, hepatic encephalopathy, ascites, hepatomegaly, blood bilirubin increased, hepatic function abnormal, hepatic enzymes increased.

Immune: immunosuppression, anaphylactic shock and hypersensitivity reaction.

Infections: The following manifestations have been associated with myelosuppression and immunosuppression caused by cyclophosphamide: increased risk for and severity of pneumonias (including fatal outcomes), other bacterial, fungal, viral, protozoal and, parasitic infections; reactivation of latent infections, (including viral hepatitis, tuberculosis), Pneumocystis jiroveci, herpes zoster, Strongyloides, sepsis and septic shock.

Investigations: blood lactate dehydrogenase increased, C-reactive protein increased.

Metabolism and Nutrition: hyponatremia, fluid retention, blood glucose increased, blood glucose decreased.

Musculoskeletal and Connective Tissue: rhabdomyolysis, scleroderma, muscle spasms, myalgia, arthralgia.

Neoplasms: acute leukemia, myelodysplastic syndrome, lymphoma, sarcomas, renal cell carcinoma, renal pelvis cancer, bladder cancer, ureteric cancer, thyroid cancer.

Nervous System: encephalopathy, convulsion, dizziness, neurotoxicity has been reported and manifested as reversible posterior leukoencephalopathy syndrome, myelopathy, peripheral neuropathy, polyneuropathy, neuralgia, dysesthesia, hypoesthesia, paresthesia, tremor, dysgeusia, hypogeusia, parosmia.

Pregnancy: premature labor.

Psychiatric: confusional state.

Renal and Urinary: renal failure, renal tubular disorder, renal impairment, nephropathy toxic, hemorrhagic cystitis, bladder necrosis, cystitis ulcerative, bladder contracture, hematuria, nephrogenic diabetes insipidus, atypical urinary bladder epithelial cells.

Reproductive System: infertility, ovarian failure, ovarian disorder, amenorrhea, oligomenorrhea, testicular atrophy, azoospermia, oligospermia.

Respiratory: pulmonary veno-occlusive disease, acute respiratory distress syndrome, interstitial lung disease as manifested by respiratory failure (including fatal outcomes), obliterative bronchiolitis, organizing pneumonia, alveolitis allergic, pneumonitis, pulmonary hemorrhage; respiratory distress, pulmonary hypertension, pulmonary edema, pleural effusion, bronchospasm, dyspnea, hypoxia, cough, nasal congestion, nasal discomfort, oropharyngeal pain, rhinorrhea.

Skin and Subcutaneous Tissue: toxic epidermal necrolysis, Stevens-Johnson syndrome, erythema multiforme, palmar-plantar erythrodysesthesia syndrome, radiation recall dermatitis, toxic skin eruption, urticaria, dermatitis, blister, pruritus, erythema, nail disorder, facial swelling, hyperhidrosis, alopecia.

Tumor lysis syndrome: like other cytotoxic drugs, cyclophosphamide may induce tumor-lysis syndrome and hyperuricemia in patients with rapidly growing tumors.

Vascular: pulmonary embolism, venous thrombosis, vasculitis, peripheral ischemia, hypertension, hypotension, flushing, hot flush.

7 DRUG INTERACTIONS

7.1 Effect of Other Drugs on Cyclophosphamide Exposure

Protease Inhibitors

Concomitant use of protease inhibitors may increase the concentration of cytotoxic metabolites and may enhance the toxicities of cyclophosphamide, including higher incidence of infections, neutropenia, and mucositis. Monitor for increased toxicities in patients receiving protease inhibitors.

7.2 Drugs that Potentiate Cyclophosphamide Toxicities

Drugs or agents with similar toxicities to FRINDOVYX and can potentiate these effects are listed in Table 2.

Table 2: Drugs that Potentiate Cyclophosphamide Toxicities
Toxicity | Drugs
Increased hematotoxicity and/or immunosuppression | ● ACE inhibitors: ACE inhibitors can cause leukopenia. ● Natalizumab ● Paclitaxel: Increased hematotoxicity has been reported when cyclophosphamide was administered after paclitaxel infusion. ● Thiazide diuretics ● Zidovudine
Increased cardiotoxicity | ● Anthracyclines ● Cytarabine ● Pentostatin ● Radiation therapy of the cardiac region ● Trastuzumab
Increased pulmonary toxicity | ● Amiodarone ● G-CSF, GM-CSF (granulocyte colony-stimulating factor, granulocyte macrophage colony-stimulating factor)
Increased nephrotoxicity | ● Amphotericin B ● Indomethacin: Acute water intoxication has been reported with concomitant use of indomethacin
Increase in other toxicities: | ● Azathioprine: Increased risk of hepatotoxicity (liver necrosis) ● Busulfan: Increased incidence of hepatic veno-occlusive disease and mucositis has been reported. ● Protease inhibitors: Increased incidence of mucositis
Increased risk of hemorrhagic cystitis | ● Radiation treatment: Increased risk of hemorrhagic cystitis may result from a combined effect of cyclophosphamide and past or concomitant radiation treatment.

7.3 Effect of Cyclophosphamide on Other Drugs

Metronidazole

Acute encephalopathy has been reported in a patient receiving cyclophosphamide and metronidazole. Monitor for neurologic toxicities in patients receiving metronidazole.

Tamoxifen

Concomitant use of tamoxifen and a cyclophosphamide-containing chemotherapy regimen may increase the risk of thromboembolic complications. Monitor for signs and symptoms of thromboembolic events in patients receiving tamoxifen.

Coumarins

Both increased and decreased warfarin effect have been reported in patients receiving warfarin and cyclophosphamide. Monitor anticoagulant activity closely in patients receiving warfarin or other coumarins.

Cyclosporine

Concomitant administration of cyclophosphamide may decrease serum concentrations of cyclosporine. This interaction may result in an increased incidence of graft-versus-host disease. Monitor for signs and symptoms of graft-versus-host disease in patients receiving cyclosporine.

Depolarizing Muscle Relaxants

If a patient has been treated with cyclophosphamide within 10 days of general anesthesia, alert the anesthesiologist.

Cyclophosphamide causes a marked and persistent inhibition of cholinesterase activity. Prolonged apnea may occur with concurrent depolarizing muscle relaxants (e.g., succinylcholine).

8 USE IN SPECIFIC POPULATIONS

8.1 Pregnancy

Risk Summary

Based on its mechanism of action and published reports of effects in pregnant patients or animals, FRINDOVYX can cause fetal harm when administered to a pregnant woman [see Clinical Pharmacology (12.1) and Nonclinical Toxicology (13.1)]. Exposure to cyclophosphamide during pregnancy may cause fetal malformations, miscarriage, fetal growth retardation, and toxic effects in the newborn [see Data]. Cyclophosphamide is teratogenic and embryo-fetal toxic in mice, rats, rabbits and monkeys [see Data]. Advise pregnant women and females of reproductive potential of the potential risk to a fetus.

The estimated background risk of major birth defects and miscarriage for the indicated population is unknown. In the U.S. general population, the estimated background risk of major birth defects is 2% - 4% and of miscarriage is 15% - 20% of clinically recognized pregnancies.

Data

Human Data

Malformations of the skeleton, palate, limbs and eyes as well as miscarriage have been reported after exposure to cyclophosphamide in the first trimester. Fetal growth retardation and toxic effects manifesting in the newborn, including leukopenia, anemia, pancytopenia, severe bone marrow hypoplasia, and gastroenteritis have been reported after exposure to cyclophosphamide.

Animal Data

Administration of cyclophosphamide to pregnant mice, rats, rabbits and monkeys during the period of organogenesis at doses at or below the dose in patients based on body surface area resulted in various malformations, which included neural tube defects, limb and digit defects and other skeletal anomalies, cleft lip and palate, and reduced skeletal ossification.

8.2 Lactation

Risk Summary

Cyclophosphamide is present in breast milk. Neutropenia, thrombocytopenia, low hemoglobin, and diarrhea have been reported in infants breast fed by women treated with cyclophosphamide. Because of the potential for serious adverse reactions in a breastfed child, advise lactating women not to breastfeed during treatment with FRINDOVYX and for 1 week after the last dose.

8.3 Females and Males of Reproductive Potential

FRINDOVYX can cause fetal harm when administered to a pregnant woman [see Use in Specific Populations (8.1)].

Pregnancy Testing

Verify the pregnancy status of females of reproductive potential prior to the initiation of FRINDOVYX [see Use in Specific Populations (8.1)].

Contraception

Females

Advise females of reproductive potential to use effective contraception during treatment with FRINDOVYX and for up to 1 year after completion of therapy.

Males

Based on findings in genetic toxicity and animal reproduction studies, advise male patients with female partners of reproductive potential to use effective contraception during treatment with FRINDOVYX and for 4 months after completion of therapy [see Nonclinical Toxicology (13.1)].

Infertility

Females

Amenorrhea, transient or permanent, associated with decreased estrogen and increased gonadotropin secretion develops in a proportion of women treated with cyclophosphamide. Affected patients generally resume regular menses within a few months after cessation of therapy. The risk of premature menopause with cyclophosphamide increases with age. Oligomenorrhea has also been reported in association with cyclophosphamide treatment.

Animal data suggest an increased risk of failed pregnancy and malformations may persist after discontinuation of cyclophosphamide as long as oocytes/follicles exist that were exposed to cyclophosphamide during any of their maturation phases. The exact duration of follicular development in humans is not known, but may be longer than 12 months [see Nonclinical Toxicology (13.1)].

Males

Men treated with cyclophosphamide may develop oligospermia or azoospermia which are normally associated with increased gonadotropin but normal testosterone secretion.

8.4 Pediatric Use

The safety and effectiveness of FRINDOVYX have been established in pediatric patients and information on this use is discussed throughout the labeling.

The alcohol content of FRINDOVYX should be taken into account when given to pediatric patients [see Warnings and Precautions (5.7)].

Pre-pubescent females who receive cyclophosphamide generally develop secondary sexual characteristics normally and have regular menses. Ovarian fibrosis with apparently complete loss of germ cells after prolonged administration of cyclophosphamide in late pre-pubescence has been reported. Females who received cyclophosphamide who have retained ovarian function after completing treatment are at increased risk of developing premature menopause.

Pre-pubescent males who receive cyclophosphamide develop secondary sexual characteristics normally, but may have oligospermia or azoospermia and increased gonadotropin secretion. Some degree of testicular atrophy may occur. Cyclophosphamide-induced azoospermia is reversible in some patients, though the reversibility may not occur for several years after cessation of therapy.

8.5 Geriatric Use

There is insufficient data from clinical studies of cyclophosphamide available for patients 65 years of age and older to determine whether they respond differently than younger patients. In general, dose selection for an elderly patient should be cautious, usually starting at the low end of the dosing range, reflecting the greater frequency of decreased hepatic, renal, or cardiac functioning, and of concomitant disease or other drug therapy.

8.6 Renal Impairment

In patients with severe renal impairment, decreased renal excretion may result in increased plasma levels of cyclophosphamide and its metabolites which may increase toxicity [see Clinical Pharmacology (12.3)]. Monitor patients with severe renal impairment (CLcr =10 mL/min to 24 mL/min) for signs and symptoms of toxicity.

Cyclophosphamide and its metabolites are dialyzable although there are probably quantitative differences depending upon the dialysis system. In patients requiring dialysis, consider using a consistent interval between cyclophosphamide administration and dialysis.

8.7 Hepatic Impairment

Patients with severe hepatic impairment have reduced conversion of cyclophosphamide to the active 4-hydroxyl metabolite, potentially reducing efficacy [see Clinical Pharmacology (12.3)]. Monitor patients with severe hepatic impairment (total bilirubin > 3 x ULN and any aspartate aminotransferase (AST)) for reduced effectiveness of cyclophosphamide.

The alcohol content of FRINDOVYX should be taken into account when given to patients with hepatic impairment [see Warnings and Precautions (5.7)].

10 OVERDOSAGE

No specific antidote for cyclophosphamide is known.

Overdosage should be managed with supportive measures, including appropriate treatment for any concurrent infection, myelosuppression, or cardiac toxicity should it occur.

Serious consequences of overdosage include manifestations of dose dependent toxicities such as myelosuppression, urotoxicity, cardiotoxicity (including cardiac failure), veno-occlusive hepatic disease, and stomatitis [see Warnings and Precautions (5.1, 5.2, 5.3, and 5.6)].

Patients who received an overdose should be closely monitored for the development of toxicities, and hematologic toxicity in particular.

Cyclophosphamide and its metabolites are dialyzable. Therefore, rapid hemodialysis is indicated when treating any suicidal or accidental overdose or intoxication [see Clinical Pharmacology (12.3)].

Cystitis prophylaxis with mesna may be helpful in preventing or limiting urotoxic effects with cyclophosphamide overdose.

11 DESCRIPTION

Cyclophosphamide is an alkylating drug. It is an antineoplastic drug chemically related to the nitrogen mustards. The chemical name for cyclophosphamide is (±)-2-[Bis(2-chloroethyl)amino]tetrahydro-2H-1,3,2-oxazaphosphorine 2-oxide monohydrate, and has the following structural formula:

Cyclophosphamide is a white crystalline powder with the molecular formula C7H15Cl2N2O2 P•H2O and a molecular weight of 279.1. Cyclophosphamide is soluble in water, saline, or ethanol. The pKa of cyclophosphamide is 5.7.

FRINDOVYX is a clear, colorless to slight yellow sterile solution available as 500 mg/mL, 1 g/2 mL, and 2 g/4 mL in multiple dose vial for dilution prior to intravenous administration.

- 500 mg/mL vial contains 534.5 mg cyclophosphamide monohydrate, equivalent to 500 mg cyclophosphamide and 500 mg dehydrated alcohol (equivalent to 63% v/v).
- 1 g/2 mL vial contains 1069.0 mg cyclophosphamide monohydrate equivalent to 1 g cyclophosphamide and 1000 mg dehydrated alcohol (equivalent to 63% v/v).
- 2 g/4 mL vial contains 2138.0 mg cyclophosphamide monohydrate, equivalent to 2 g cyclophosphamide and 2000 mg dehydrated alcohol (equivalent to 63% v/v).

12 CLINICAL PHARMACOLOGY

12.1 Mechanism of Action

The mechanism of action has not been fully characterized. However, cross-linking of tumor cell DNA may be involved.

The active alkylating metabolites of cyclophosphamide interfere with the growth of susceptible rapidly proliferating malignant cells.

12.2 Pharmacodynamics

Cyclophosphamide exposure-response relationships and the time course of pharmacodynamic response have not been fully characterized.

12.3 Pharmacokinetics

Cyclophosphamide is a prodrug. Cyclophosphamide pharmacokinetics are linear over the approved recommended dose range.

Distribution

The volume of distribution of cyclophosphamide is 30 to 50 L. Cyclophosphamide is approximately 20% protein bound, with no dose dependent changes. Some metabolites are greater than 60% protein bound.

Elimination

The elimination half-life (t½) of cyclophosphamide ranges from 3 to 12 hours, and the clearance (CL) ranges from 4 to 5.6 L/h.

When cyclophosphamide was administered at 4 g/m^2 (approximately 2 times the approved recommended dosage) over a 90-minutes infusion, concentration-time data demonstrate saturable elimination in parallel with first-order renal elimination.

Metabolism

Cyclophosphamide is metabolized by cytochrome P450s including CYP2A6, 2B6, 3A, 2C9, and 2C19. Cyclophosphamide is activated to form 4-hydroxycyclophosphamide, which is in equilibrium with its ring-open tautomer aldophosphamide. 4-hydroxycyclophosphamide and aldophosphamide can undergo oxidation by aldehyde dehydrogenases to form the inactive metabolites 4-ketocyclophosphamide and carboxyphosphamide, respectively. Aldophosphamide can undergo β-elimination to form active metabolites phosphoramide mustard and acrolein. This spontaneous conversion can be catalyzed by albumin and other proteins. At high doses, the fraction of parent compound cleared by 4-hydroxylation is reduced resulting in non-linear elimination of cyclophosphamide.

Cyclophosphamide appears to induce its own metabolism. This auto-induction results in an increase in CL, increased formation of active 4-hydroxycyclophosphamide and shortened t½ following multiple doses administered at 12-to 24-hour interval.

Excretion

Cyclophosphamide and its metabolites are eliminated by hepatic and renal pathways. Cyclophosphamide is primarily excreted as metabolites. Ten to 20% is excreted unchanged in the urine. A small percentage of cyclophosphamide may be eliminated unchanged in bile.

Specific Populations

Renal Impairment

Following one-hour intravenous infusion, cyclophosphamide AUC increased by 38% in patients with CLcr of 25 to 50 mL/min, by 77% in patients with CLcr of 10 to 24 mL/min and by 23% in the hemodialysis group (CLcr of < 10 mL/min) compared to the control group (CLcr≥ 80 mL/min).

Cyclophosphamide is dialyzable. Dialysis clearance averaged 104 mL/min, which is similar to the metabolic clearance of 95 mL/min for cyclophosphamide. A mean of 37% of the administered dose of cyclophosphamide was removed during a 4-hour hemodialysis period. The t½ was 3.3 hours in patients during hemodialysis, a 49% reduction compared to t½ of 6.5 hours in uremic patients.

Hepatic Impairment

Cyclophosphamide CL is decreased by 40% (45 ± 8.6 L/kg) and t½ is prolonged by 64% (12.5 ± 1 hours) in patients with hepatic impairment with a mean bilirubin 3.5 mg/dL and mean AST 90 IU/L compared to patients with normal hepatic function (mean bilirubin 0.5 mg/dL, mean AST 10 IU/L).

13 NONCLINICAL TOXICOLOGY

13.1 Carcinogenesis, Mutagenesis, Impairment of Fertility

Cyclophosphamide administered by different routes, including intravenous, subcutaneous or intraperitoneal injection, or in drinking water, caused tumors in both mice and rats. In addition to leukemia and lymphoma, benign and malignant tumors were found at various tissue sites, including urinary bladder, mammary gland, lung, liver, and injection site [see Warnings and Precautions (5.5)].

Cyclophosphamide was mutagenic and clastogenic in multiple in vitro and in vivo genetic toxicology studies.

Cyclophosphamide is genotoxic in male and female germ cells. Animal data indicate that exposure of oocytes to cyclophosphamide during follicular development may result in a decreased rate of implantations and viable pregnancies, and in an increased risk of malformations. Male mice and rats treated with cyclophosphamide show alterations in male reproductive organs (e.g., decreased weights, atrophy, changes in spermatogenesis), and decreases in reproductive potential (e.g., decreased implantations and increased post-implantation loss) and increases in fetal malformations when mated with untreated females [see Use in Specific Populations (8.3)].

15 REFERENCES

1. OSHA Hazardous Drugs. OSHA. http://www.osha.gov/SLTC/hazardousdrugs/index.html.

16 HOW SUPPLIED/STORAGE AND HANDLING

FRINDOVYXTM is a ready-to-dilute clear, colorless to slight yellow sterile solution containing cyclophosphamide and is supplied in multiple-dose vial.

FRINDOVYXTM Injection

NDC Number | Strength | Vial Presentation
83831-119-01 | 500 mg/mL | Multiple-dose vial, carton of 1
83831-120-02 | 1 g/2 mL | Multiple-dose vial, carton of 1
83831-121-04 | 2 g/4 mL | Multiple-dose vial, carton of 1

Store vials refrigerated at 2°C to 8°C (36°F to 46°F).

Store diluted solutions of cyclophosphamide according to Table 1 [see Dosage and Administration (2.3)].

Cyclophosphamide is a hazardous product. Follow special handling and disposal procedures.^1

17 PATIENT COUNSELING INFORMATION

Advise the patient of the following:

Myelosuppression, Immunosuppression, and Infections

● Inform patients of the possibility of myelosuppression, immunosuppression, and infections (sometimes fatal). Explain the need for routine blood cell counts. Instruct patients to monitor their temperature frequently and immediately report any occurrence of fever [see Warnings and Precautions (5.1)].

Urinary Tract and Renal Toxicity

● Advise the patient to report urinary symptoms (patients should report if their urine has turned a pink or red color) and the need for increasing fluid intake and frequent voiding [see Warnings and Precautions (5.2)].

Cardiotoxicity

● Inform patients of the possibility of cardiotoxicity (which may be fatal).

● Advise patients to contact a health care professional immediately for any of the following: new onset or worsening shortness of breath, cough, swelling of the ankles/legs, palpitations, weight gain of more than 5 pounds in 24 hours, dizziness or loss of consciousness [see Warnings and Precautions (5.3)].

Pulmonary Toxicity

● Warn patients of the possibility of developing non-infectious pneumonitis. Advise patients to report promptly any new or worsening respiratory symptoms [see Warnings and Precautions (5.4)].

Secondary Malignancies

● Inform patients that there is an increased risk of secondary malignancies with FRINDOVYX [see Warnings and Precautions (5.5)].

Alcohol Content

● Explain to patients the possible effects of the alcohol content in FRINDOVYX, including possible effects on the central nervous system. Patients in whom alcohol should be avoided or minimized should consider the alcohol content of FRINDOVYX. Alcohol could impair their ability to drive or use machines immediately after infusion [see Warnings and Precautions (5.7)].

Embryo-Fetal Toxicity

● Inform female patients of the risk to a fetus and potential loss of pregnancy. Advise females to inform their healthcare provider of a known or suspected pregnancy [see Warnings and Precautions (5.8) and Use in Specific Populations (8.1)].

● Advise female patients of reproductive potential to use effective contraception during treatment and for up to 1 year after completion of therapy [see Warnings and Precautions (5.8) and Use in Specific Populations (8.1, 8.3)].

● Advise male patients with female partners of reproductive potential to use effective contraception during treatment and for 4 months after completion of therapy [see Warnings and Precautions (5.8) and Use in Specific Populations (8.1, 8.3)].

Lactation

● Advise lactating women not to breastfeed during treatment and for 1 week after the last dose of FRINDOVYX [see Use in Specific Populations (8.2)].

Infertility

● Advise males and females of reproductive potential that FRINDOVYX may impair fertility [see Warnings and Precautions (5.9) and Use in Specific Populations (8.3, 8.4)].

Common Adverse Reactions

● Explain to patients that side effects such as nausea, vomiting, stomatitis, impaired wound healing, amenorrhea, premature menopause, sterility and hair loss may be associated with cyclophosphamide administration. Other undesirable effects (including, e.g., dizziness, blurred vision, visual impairment) could affect the ability to drive or use machines [see Adverse Reactions (6.1)].

Hydration and Important Administration Instructions

● Advise the patients that during or immediately after the administration, adequate amounts of fluid are required to reduce the risk of urinary tract toxicity [see Dosage and Administration (2.1)].

Manufactured for:
Avyxa Pharma, LLC
New Jersey 07054, USA
Made in India

PACKAGE LABEL.PRINCIPAL DISPLAY PANEL

Frindovyx (cyclophosphamide) Injection, 500mg/mL - Vial Label
Frindovyx (cyclophosphamide) Injection, 500 mg/ mL - Carton Label
Frindovyx (cyclophosphamide) Injection, 1 g/2 mL - Vial Label
Frindovyx (cyclophosphamide) Injection, 2 g/4 mL - Vial Label
Frindovyx (cyclophosphamide) Injection, 2 g/ 4 mL - Carton Label